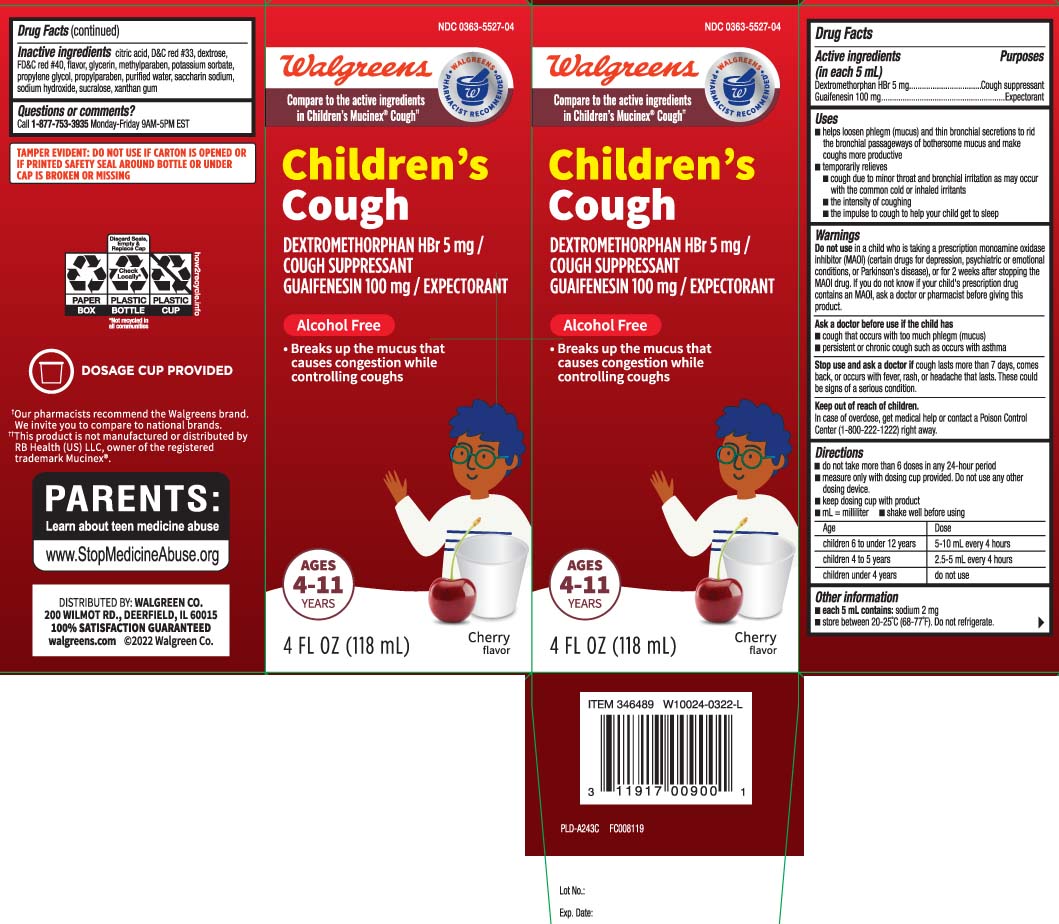 DRUG LABEL: Mucus Relief Cough
NDC: 0363-5527 | Form: LIQUID
Manufacturer: Walgreens
Category: otc | Type: HUMAN OTC DRUG LABEL
Date: 20240508

ACTIVE INGREDIENTS: DEXTROMETHORPHAN HYDROBROMIDE 5 mg/5 mL; GUAIFENESIN 100 mg/5 mL
INACTIVE INGREDIENTS: ANHYDROUS CITRIC ACID; D&C RED NO. 33; DEXTROSE; FD&C RED NO. 40; GLYCERIN; METHYLPARABEN; POTASSIUM SORBATE; PROPYLENE GLYCOL; PROPYLPARABEN; WATER; SACCHARIN SODIUM; SODIUM HYDROXIDE; SUCRALOSE; XANTHAN GUM

Drug Facts

Active ingredients (in each 5 mL)

Dextromethorphan HBr 5 mg

Guaifenesin 100 mg

Purposes

Cough suppressant

Expectorant

Uses

- helps loosen phlegm (mucus) and thin bronchial secretions to rid the bronchial passageways of bothersome mucus and make coughs more productive
- temporarily relieves:
  - cough due to minor throat and bronchial irritation as may occur with the common cold or inhaled irritants
  - the intensity of coughing
  - the impulse to cough to help your child get to sleep

Warnings

Do not use

in a child who is taking a prescription monoamine oxidase inhibitor (MAOI) (certain drugs for depression, psychiatric or emotional conditions, or Parkinson's disease), or for 2 weeks after stopping the MAOI drug. If you do not know if your child's prescription drug contains an MAOI, ask a doctor or pharmacist before taking this product.

Ask a doctor before use if the child has

- cough that occurs with too much phlegm (mucus)
- persistent or chronic cough such as occurs with asthma

Stop use and ask a doctor if

cough lasts more than 7 days, comes back, or occurs with fever, rash, or headache that lasts. These could be signs of a serious condition.

Keep out of reach of children.

In case of overdose, get medical help or contact a Poison Control Center (1-800-222-1222) right away.

Directions

- do not take more than 6 doses in any 24-hour period
- measure only with dosing cup provided. Do not use any other dosing device.
- keep dosing cup with product
- mL = milliliter
- shake well before using

age | dose
children 6 to 12 years | 5-10 mL every 4 hours
children 4 to 5 years | 2.5-5 mL every 4 hours
children under 4 years | do not use

Other information

- each 5 mL contains: sodium 2 mg
- store between 20-25ºC (68-77ºF). Do not refrigerate.

Inactive ingredients

anhydrous citric acid, D&C red #33, dextrose, FD&C red #40, flavor, glycerin, methylparaben, potassium sorbate, propylene glycol, propylparaben, purified water, saccharin sodium, sodium hydroxide, sucralose, xanthan gum

Questions or comments?

Call 1-877-753-3935 Monday-Friday 9AM-5PM EST

Principal Display Panel

Compare to active ingredients in Children's Mucinex® Cough††

Children's

Cough

DEXTROMETHORPHAN HBr 5 mg /

COUGH SUPPRESSANT

GUAIFENESIN 100 mg / EXPECTORANT

Alcohol Free

- Breaks up the mucus that causes congestion while controlling coughs

AGES 4-11 YEARS

DOSAGE CUP PROVIDED

Cherry flavor

FL OZ (mL)

††This product is not manufactured or distributed by RB Health (US) LLC, owner of the registered trademark Mucinex®.

TAMPER EVIDENT: DO NOT USE IF CARTON IS OPENED OR IF PRINTED SAFETY SEAL AROUND BOTTLE OR UNDER CAP IS BROKEN OR MISSING.

DISTRIBUTED BY: WALGREEN CO.

200 WILMOT RD., DEERFIELD, IL 60015

Package Label

WALGREENS Children's Cough Cherry Flavor